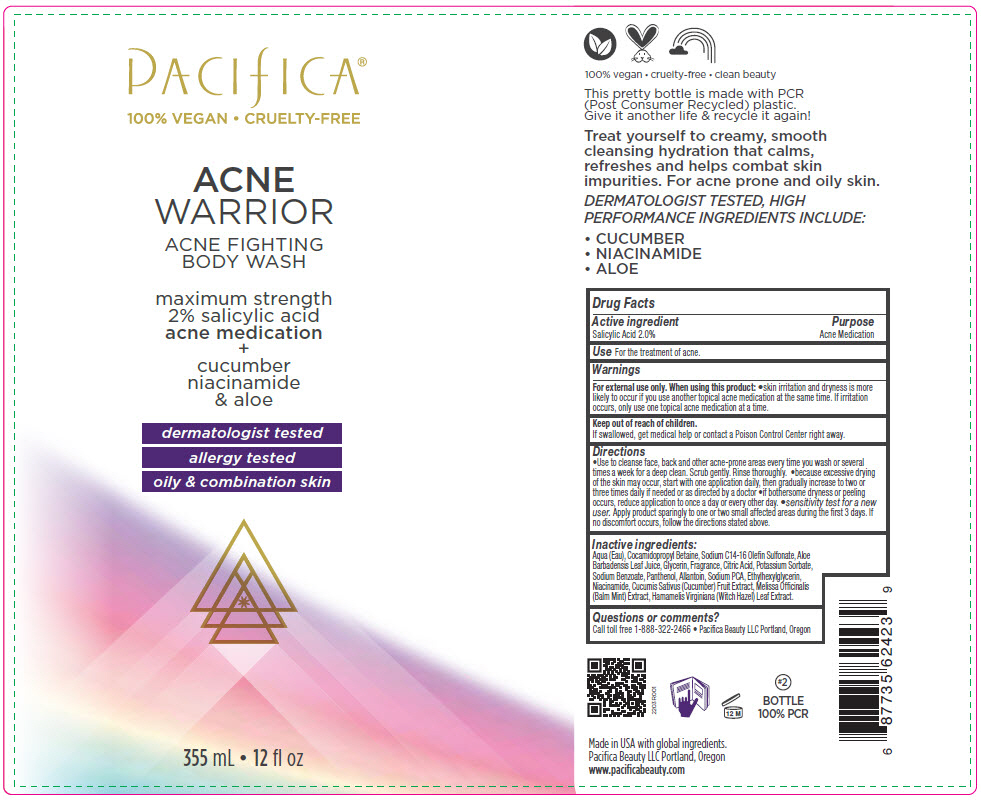 DRUG LABEL: Pacifica Acne Warrior Body Wash
NDC: 61197-012 | Form: LIQUID
Manufacturer: Pacifica Beauty LLC
Category: otc | Type: HUMAN OTC DRUG LABEL
Date: 20220607

ACTIVE INGREDIENTS: Salicylic Acid 20 mg/1 mL
INACTIVE INGREDIENTS: Water; Cocamidopropyl Betaine; Sodium C14-16 Olefin Sulfonate; Aloe Vera Leaf; Glycerin; Citric Acid Monohydrate; Potassium Sorbate; Sodium Benzoate; Panthenol; Allantoin; Sodium Pyrrolidone Carboxylate; Ethylhexylglycerin; Niacinamide; Cucumber; Melissa Officinalis Whole; Hamamelis Virginiana Leaf

Pacifica® Acne Warrior Body Wash

Drug Facts

Active ingredient

Salicylic Acid 2.0%

Purpose

Acne Medication

Use

For the treatment of acne.

Warnings

For external use only.

When using this product

- skin irritation and dryness is more likely to occur if you use another topical acne medication at the same time. If irritation occurs, only use one topical acne medication at a time.

Keep out of reach of children.

If swallowed, get medical help or contact a Poison Control Center right away.

Directions

- Use to cleanse face, back and other acne-prone areas every time you wash or several times a week for a deep clean. Scrub gently. Rinse thoroughly.
- because excessive drying of the skin may occur, start with one application daily, then gradually increase to two or three times daily if needed or as directed by a doctor
- if bothersome dryness or peeling occurs, reduce application to once a day or every other day.
- sensitivity test for a new user. Apply product sparingly to one or two small affected areas during the ﬁrst 3 days. If no discomfort occurs, follow the directions stated above.

Inactive ingredients

Aqua (Eau), Cocamidopropyl Betaine, Sodium C14-16 Oleﬁn Sulfonate, Aloe Barbadensis Leaf Juice, Glycerin, Fragrance, Citric Acid, Potassium Sorbate, Sodium Benzoate, Panthenol, Allantoin, Sodium PCA, Ethylhexylglycerin, Niacinamide, Cucumis Sativus (Cucumber) Fruit Extract, Melissa Ofﬁcinalis (Balm Mint) Extract, Hamamelis Virginiana (Witch Hazel) Leaf Extract.

Questions or comments?

Call toll free 1-888-322-2466 • Paciﬁca Beauty LLC Portland, Oregon

PRINCIPAL DISPLAY PANEL - 355 mL Bottle Label

PACIFICA®
100% VEGAN • CRUELTY-FREE

ACNE
WARRIOR

ACNE FIGHTING
BODY WASH

maximum strength
2% salicylic acid
acne medication
+
cucumber
niacinamide
& aloe

dermatologist tested
allergy tested
oily & combination skin

355 mL • 12 ﬂ oz